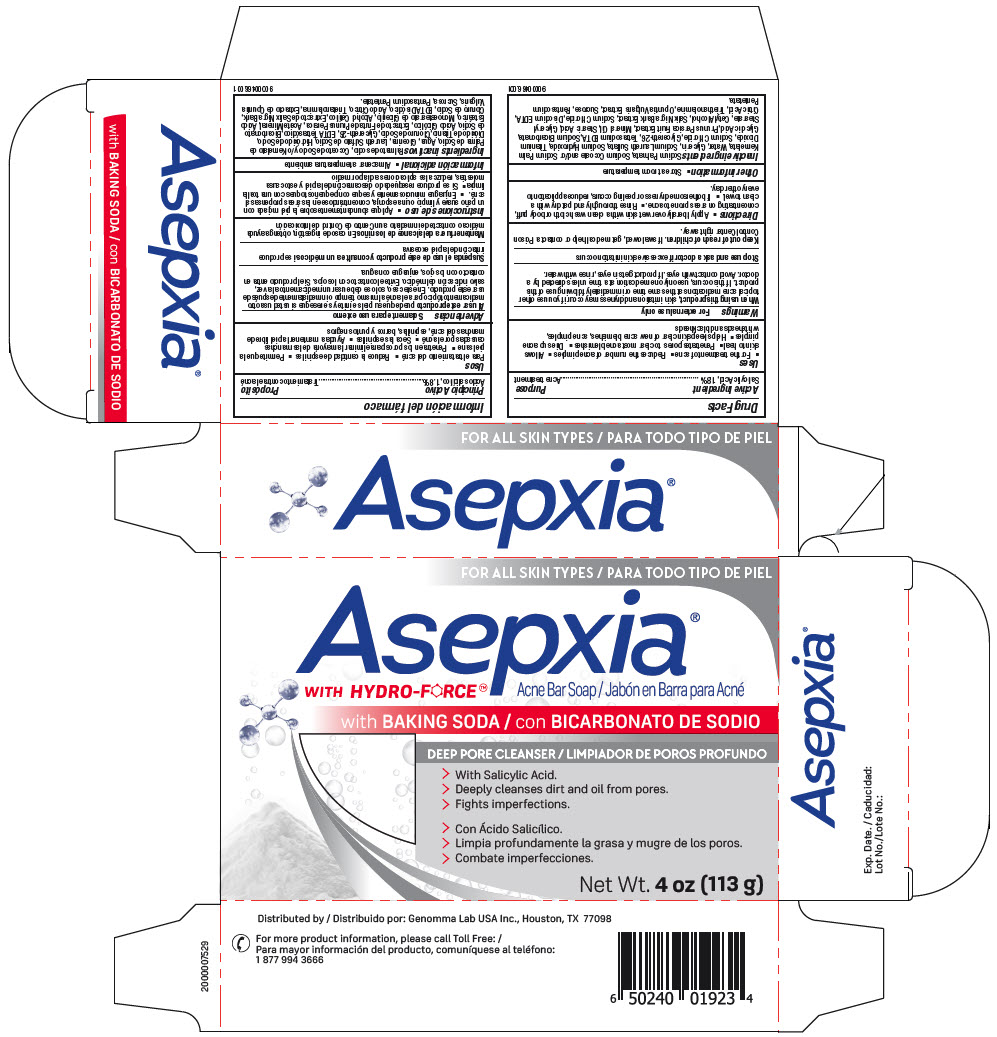 DRUG LABEL: Asepxia Baking Soda Acne Bar
NDC: 50066-810 | Form: SOAP
Manufacturer: Genomma Lab USA
Category: otc | Type: HUMAN OTC DRUG LABEL
Date: 20251201

ACTIVE INGREDIENTS: Salicylic Acid 18 mg/1 g
INACTIVE INGREDIENTS: sodium palmate; water; sodium cocoate; sodium bicarbonate; glycerin; SODIUM LAURETH-3 SULFATE

Asepxia® Baking Soda Acne Bar Soap

Drug Facts

Active Ingredient

Salicylic Acid, 1.8%

Purpose

Acne treatment

Uses

- For the treatment of acne
- Reduces the number of acne pimples
- Allows skin to heal
- Penetrates pores to clear most acne blemishes
- Dries up acne pimples
- Helps keep skin clear of new acne blemishes, acne pimples, whiteheads and blackheads

Warnings

For external use only

When using this product, skin irritation and dryness may occur if you use other topical acne medications at the same time or immediately following use of this product. If this occurs, use only one medication at a time unless directed by a doctor. Avoid contact with eyes. If product gets in eyes, rinse with water.

Stop use and ask a doctor if excessive skin irritation occurs

Keep out of reach of children. If swallowed, get medical help or contact a Poison Control Center right away.

Directions

- Apply liberally over wet skin with a clean wash cloth or body puff, concentrating on areas prone to acne.
- Rinse thoroughly and pat dry with a clean towel.
- If bothersome dryness or peeling occurs, reduce application to every other day.

Other information

- Store at room temperature

Inactive ingredients

Sodium Palmate, Sodium Cocoate and/or Sodium Palm Kernelate, Water, Glycerin, Sodium Laureth Sulfate, Sodium Hydroxide, Titanium Dioxide, Sodium Chloride, Glycereth-26, Tetrasodium EDTA, Sodium Bicarbonate, Glycolic Acid, Prunus Persica Fruit Extract, Mineral Oil, Stearic Acid, Glyceryl Stearate, Cetyl Alcohol, Salix Nigra Bark Extract, Sodium Chloride, Disodium EDTA, Citric Acid, Triethanolamine, Opuntia Vulgaris Extract, Sucrose, Pentasodium Pentetate.

Distributed by: Genomma Lab USA Inc., Houston, TX 77098

PRINCIPAL DISPLAY PANEL - 113 g Bar Carton

FOR ALL SKIN TYPES

Asepxia®
WITH HYDRO-FORCE™

Acne Bar Soap
with BAKING SODA

DEEP PORE CLEANSER

> With Salicylic Acid.
> Deeply cleanses dirt and oil from pores.
> Fights imperfections.

Net Wt. 4 oz (113 g)